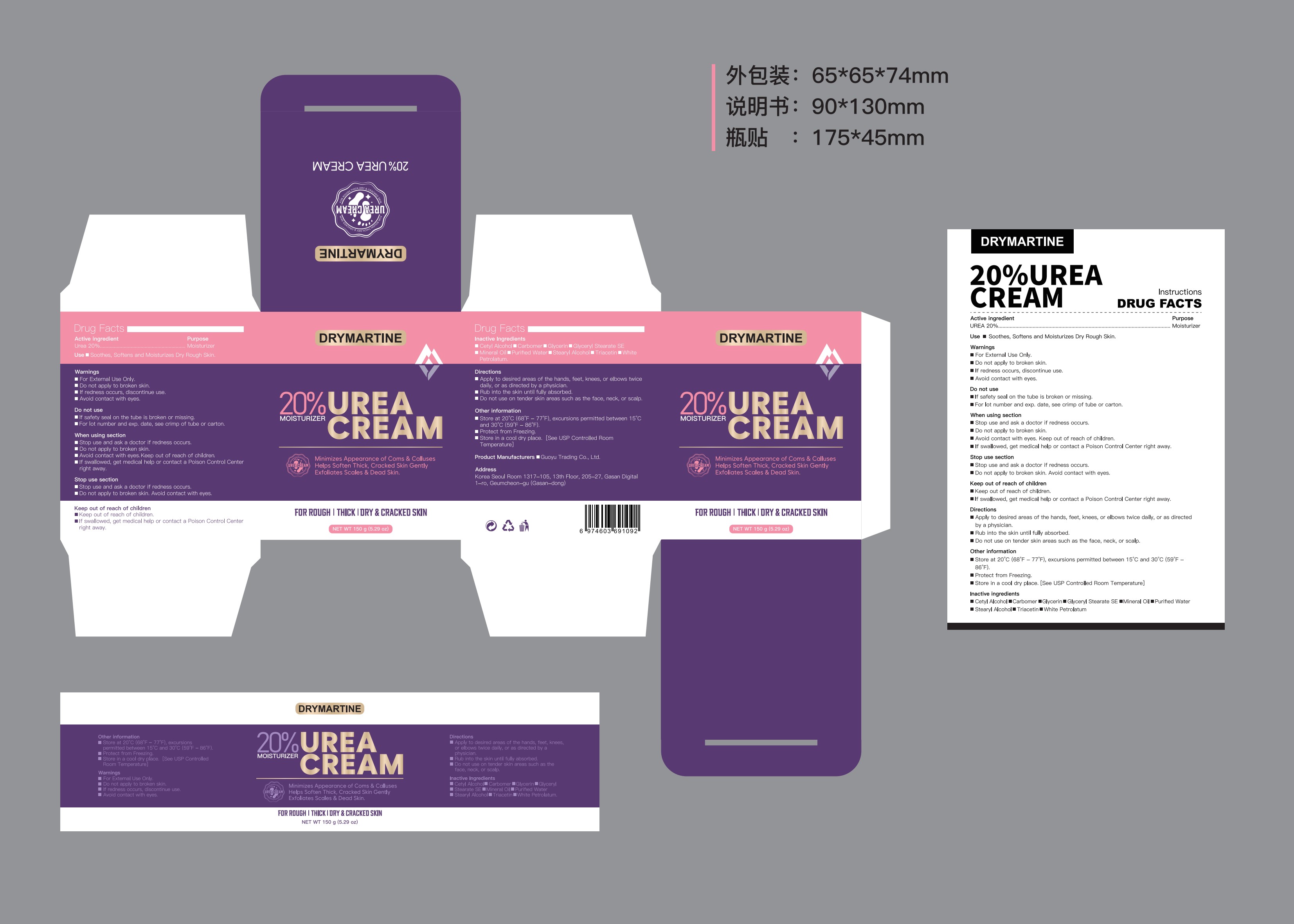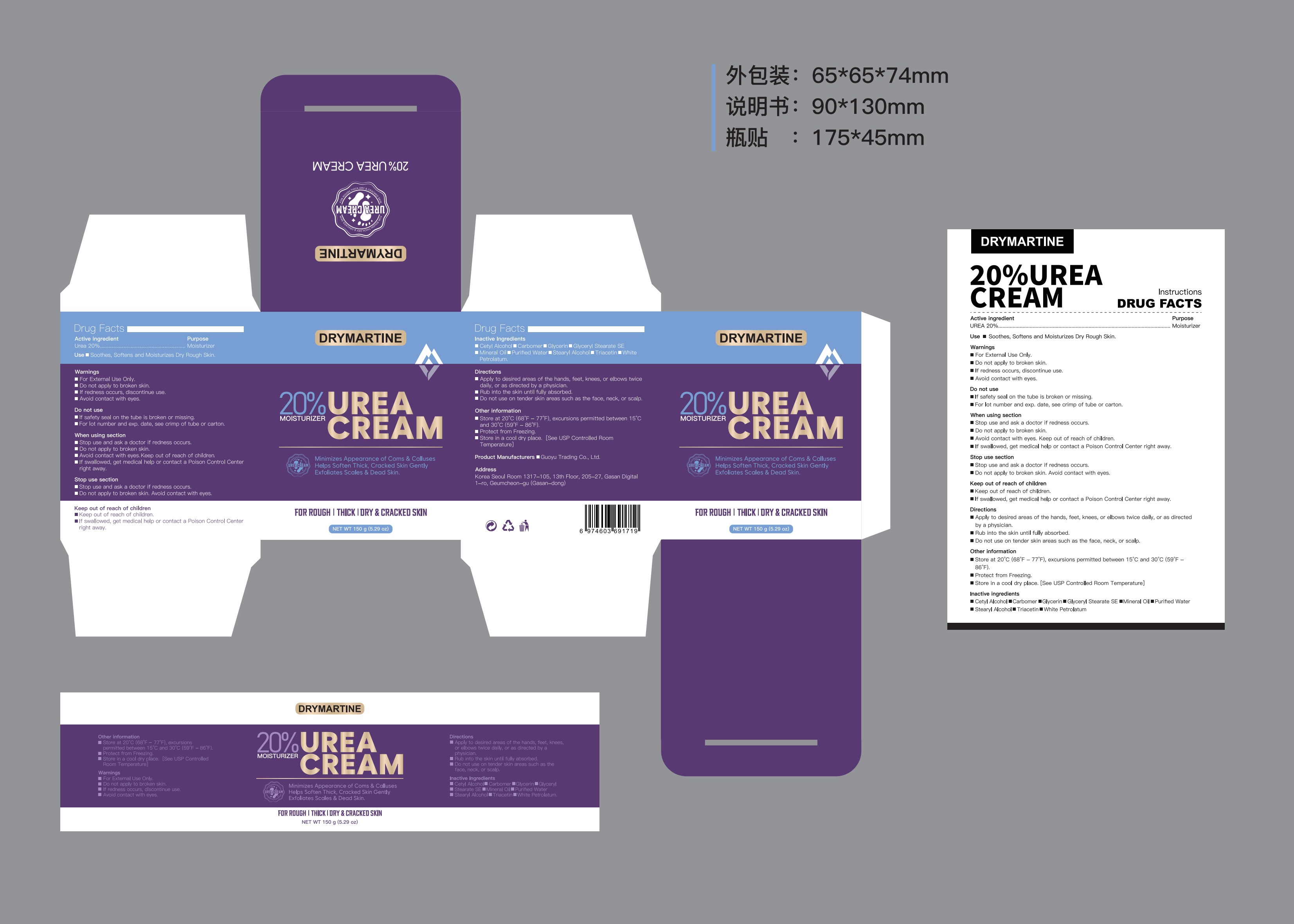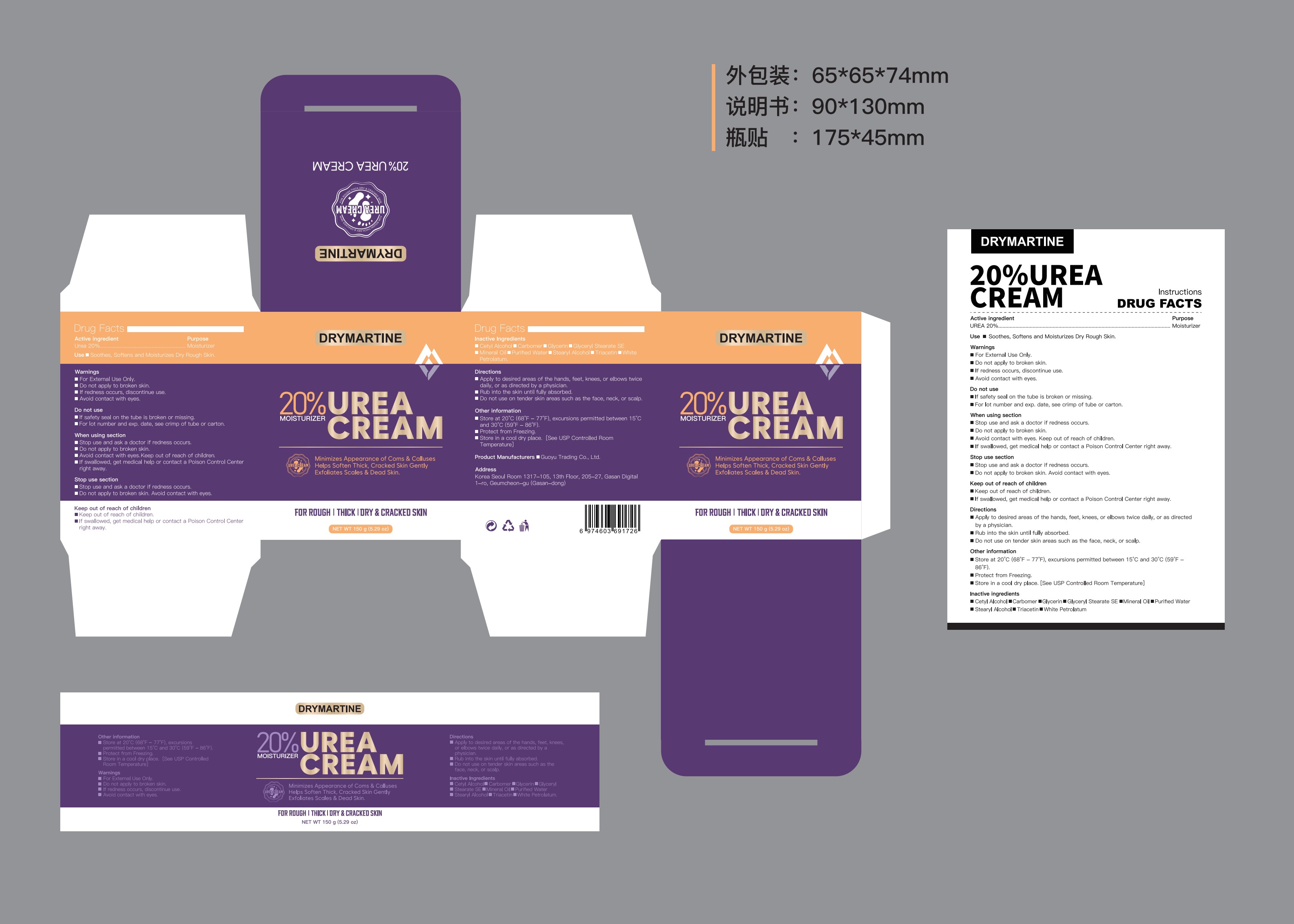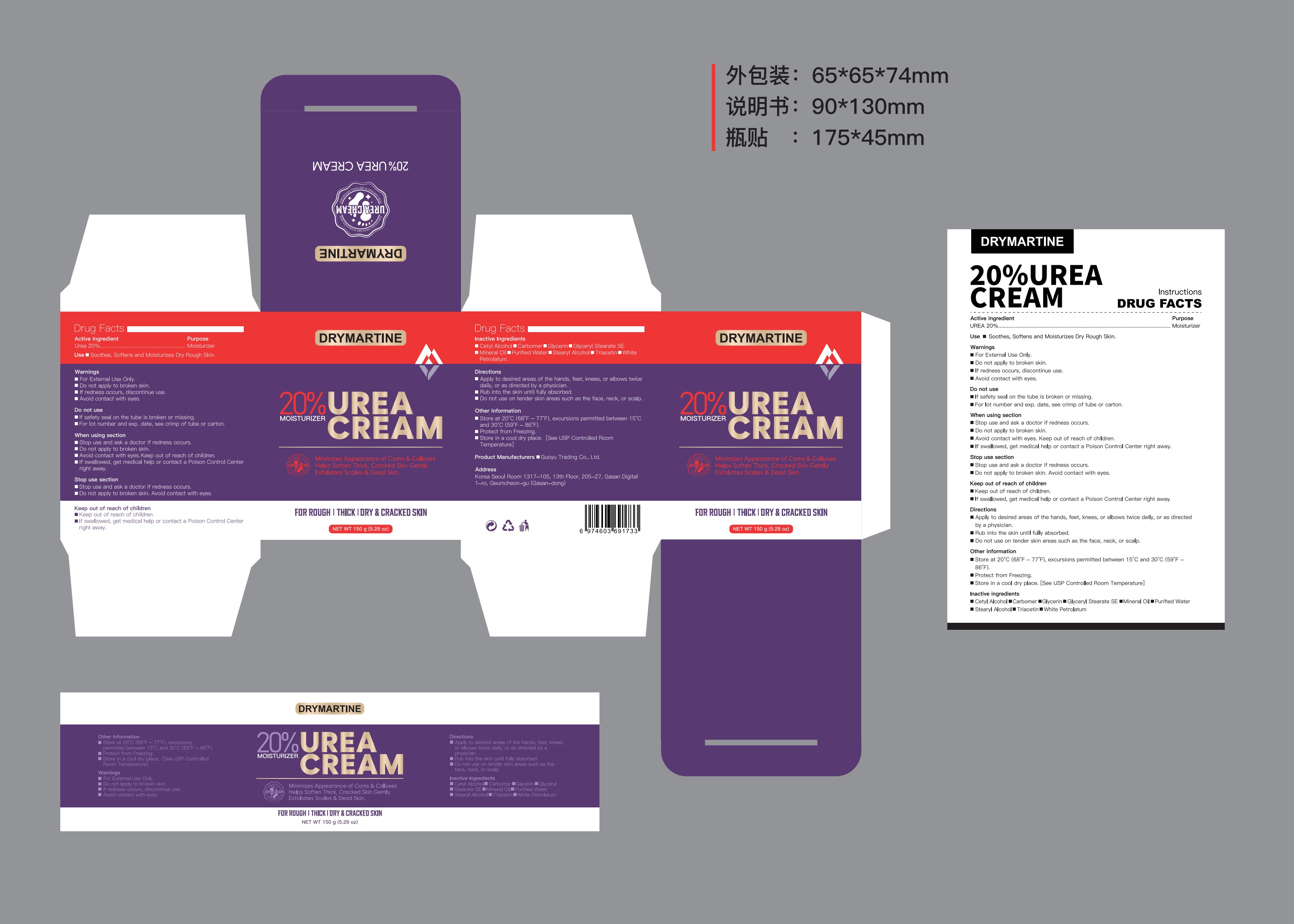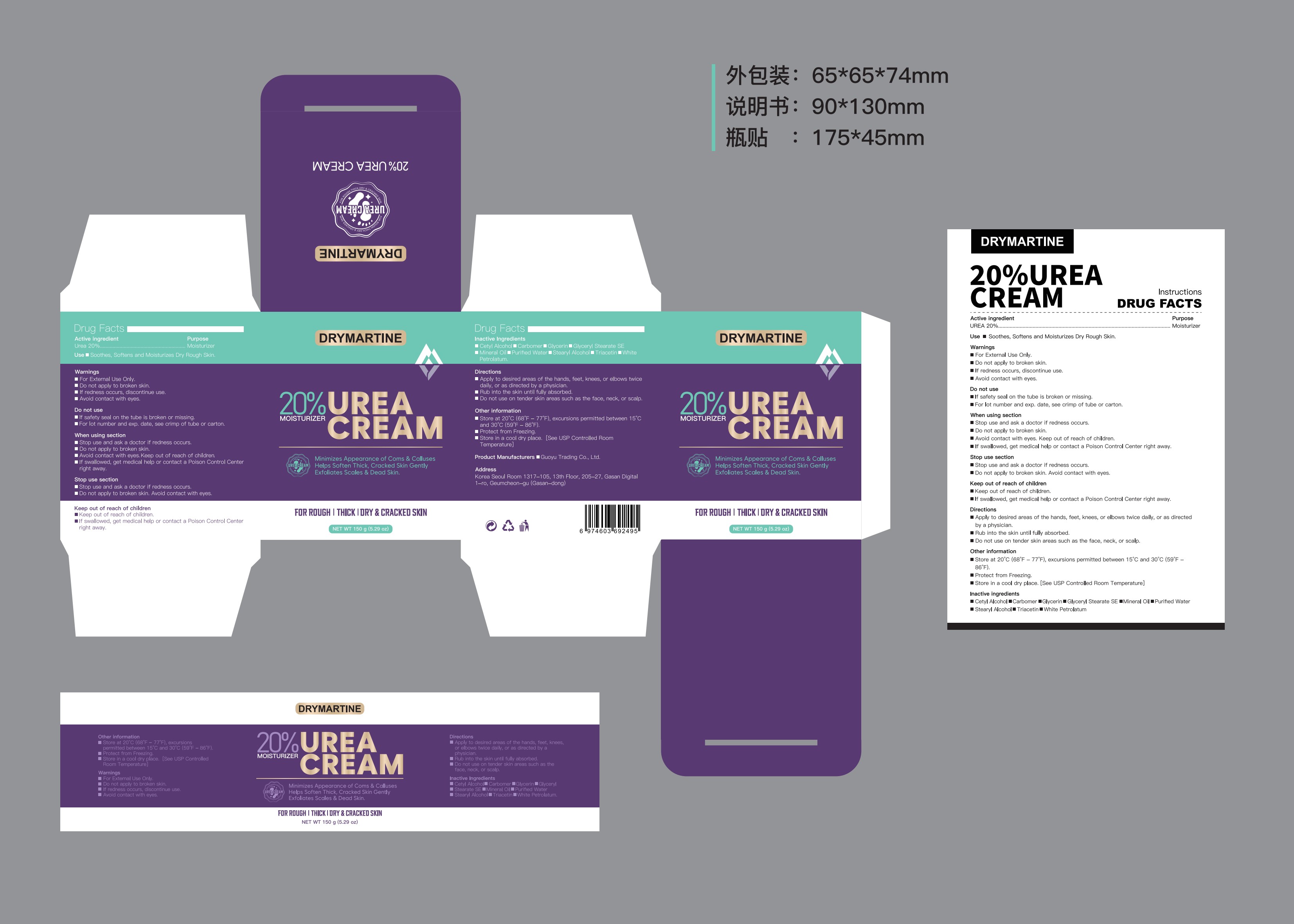 DRUG LABEL: Drymatine 20% Urea Cream
NDC: 84844-009 | Form: CREAM
Manufacturer: Guoyu Trading Co., Ltd.
Category: otc | Type: HUMAN OTC DRUG LABEL
Date: 20241105

ACTIVE INGREDIENTS: UREA 20 g/100 g
INACTIVE INGREDIENTS: GLYCERIN; GLYCERYL STEARATE SE; STEARYL ALCOHOL; CETYL ALCOHOL; CARBOMER; WHITE PETROLATUM; TRIACETIN; WATER; MINERAL OIL

84844-009

Active Ingredient

UREA 20%

Purpose

Moisturizer

Use

Soothes, Softens and Moisturizes Dry Rough Skin.

Warnings

For External Use Only.
Do not apply to broken skin. If redness occurs, discontinue use. Avoid contact with eyes.

Do not use

If safety seal on the tube is broken or missing. For lot number and exp. date, see crimp of tube or carton.

When Using

Stop use and ask a doctor if redness occurs. Do not apply to broken skin. Avoid contact with eyes.Keep out of reach of children. If swallowed, get medical help or contact a Poison Control Center right away.

Stop Use

Stop use and ask a doctor if redness occurs. Do not apply to broken skin. Avoid contact with eyes.

Ask Doctor

Stop use and ask a doctor if redness occurs.

Keep Oot Of Reach Of Children

If swallowed, get medical help or contact a Poison Control Center right away.

Directions

Apply to desired areas of the hands, feet, knees, or elbows twice daily, or as directed by a physician. Rub into the skin until fully absorbed. Do not use on tender skin areas such as the face, neck, or scalp.

Other information

Store at 20°C (68°F - 77°F), excursions permitted between 15°C and 30°C (59°F - 86°F). Protect from Freezing. Store in a cool dry place. [See USP Controlled Room Temperature]

Inactive ingredients

Cetyl Alcohol, Carbomer, Glycerin, Glyceryl Stearate SE, Mineral Oil, Purified Water, Stearyl Alcohol, Triacetin, White Petrolatum.